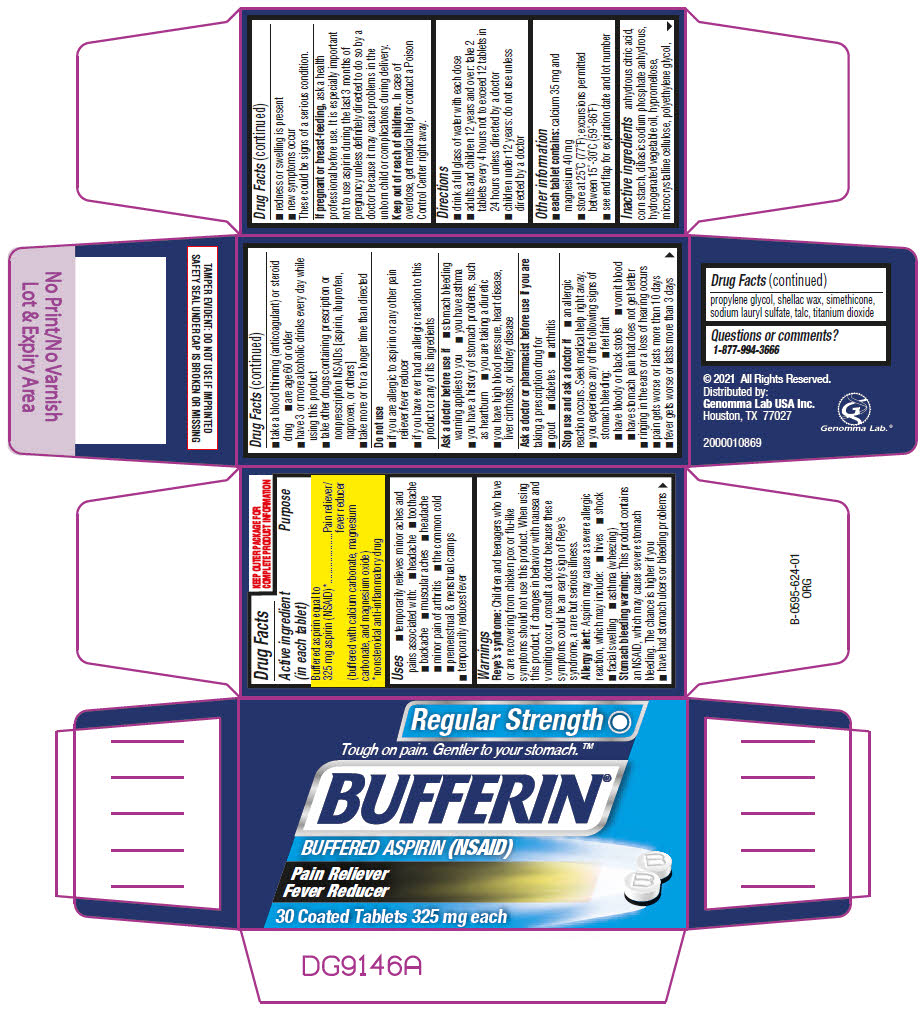 DRUG LABEL: Bufferin Regular Strength Pain Relief
NDC: 50066-610 | Form: TABLET, COATED
Manufacturer: Genomma Lab USA
Category: otc | Type: HUMAN OTC DRUG LABEL
Date: 20250225

ACTIVE INGREDIENTS: aspirin 325 mg/1 1
INACTIVE INGREDIENTS: calcium carbonate; magnesium carbonate; magnesium oxide; anhydrous citric acid; Propylene glycol; microcrystalline cellulose

Bufferin® Regular Strength Pain Relief

Drug Facts

Active ingredient (in each tablet)

Buffered aspirin equal to 325 mg aspirin (NSAID) [nonsteroidal anti-inflammatory drug] (buffered with calcium carbonate, magnesium carbonate, and magnesium oxide)

Purpose

Pain reliever/fever reducer

Uses

- temporarily relieves minor aches and pains associated with:
  - headache
  - toothache
  - backache
  - muscular aches
  - headache
  - minor pain of arthritis
  - the common cold
  - premenstrual & menstrual cramps
- temporarily reduces fever

Warnings

Reye's syndrome

Children and teenagers who have or are recovering from chicken pox or flu-like symptoms should not use this product. When using this product, if changes in behavior with nausea and vomiting occur, consult a doctor because these symptoms could be an early sign of Reye's syndrome, a rare but serious illness.

Allergy alert

Aspirin may cause a severe allergic reaction, which may include:

- hives
- shock
- facial swelling
- asthma (wheezing)

Stomach bleeding warning

This product contains an NSAID, which may cause severe stomach bleeding. The chance is higher if you

- have had stomach ulcers or bleeding problems
- take a blood thinning (anticoagulant) or steroid drug
- are age 60 or older
- have 3 or more alcoholic drinks every day while using this product
- take other drugs containing prescription or nonprescription NSAIDs [aspirin, ibuprofen, naproxen, or others]
- take more or for a longer time than directed

Do not use

- if you are allergic to aspirin or any other pain reliever/fever reducer
- if you have ever had an allergic reaction to this product or any of its ingredients

Ask a doctor before use if

- stomach bleeding warning applies to you
- you have asthma
- you have a history of stomach problems, such as heartburn
- you are taking a diuretic
- you have high blood pressure, heart disease, liver cirrhosis, or kidney disease

Ask a doctor or pharmacist before use if you are taking a prescription drug for

- gout
- diabetes
- arthritis

Stop use and ask a doctor if

- an allergic reaction occurs. Seek medical help right away.
- you experience any of the following signs of stomach bleeding:
  - feel faint
  - have bloody or black stools
  - vomit blood
  - have stomach pain that does not get better
- ringing in the ears or a loss of hearing occurs
- pain gets worse or lasts more than 10 days
- fever gets worse or lasts more than 3 days
- redness or swelling is present
- new symptoms occur

These could be signs of a serious condition.

PREGNANCY OR BREAST FEEDING

If pregnant or breast-feeding, ask a health professional before use. It is especially important not to use aspirin during the last 3 months of pregnancy unless definitely directed to do so by a doctor because it may cause problems in the unborn child or complications during delivery.

Keep out of reach of children. In case of overdose, get medical help or contact a Poison Control Center right away.

Directions

- drink a full glass of water with each dose
- adults and children 12 years and over: take 2 tablets every 4 hours not to exceed 12 tablets in 24 hours unless directed by a doctor
- children under 12 years: do not use unless directed by a doctor

Other information

- each tablet contains: calcium 35 mg and magnesium 40 mg
- store at 25°C (77°F); excursions permitted between 15°-30°C (59°-86°F)
- see end flap for expiration date and lot number

Inactive ingredients

anhydrous citric acid, corn starch, dibasic sodium phosphate anhydrous, hydrogenated vegetable oil, hypromellose, microcrystalline cellulose, polyethylene glycol, propylene glycol, shellac wax, simethicone, sodium lauryl sulfate, talc, titanium dioxide

Questions or comments?

1-877-994-3666

Distributed by:
Genomma Lab USA Inc.
Houston, TX 77027

PRINCIPAL DISPLAY PANEL - 325 mg Table Bottle Carton

Regular Strength

Tough on pain. Gentler to your stomach.™

BUFFERIN®
BUFFERED ASPIRIN (NSAID)

Pain Reliever
Fever Reducer

30 Coated Tablets 325 mg each